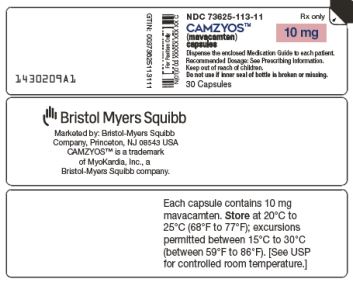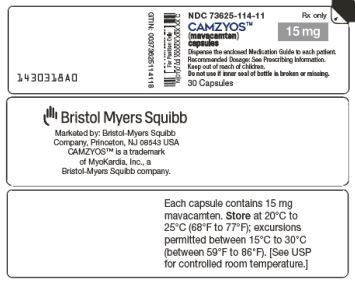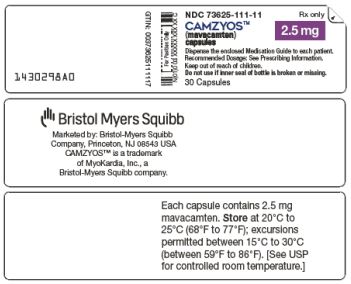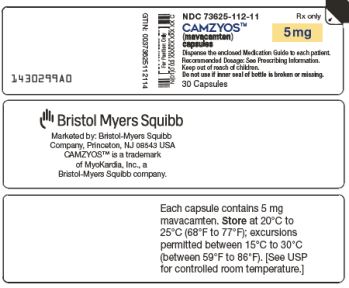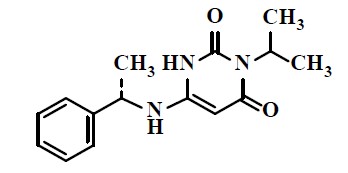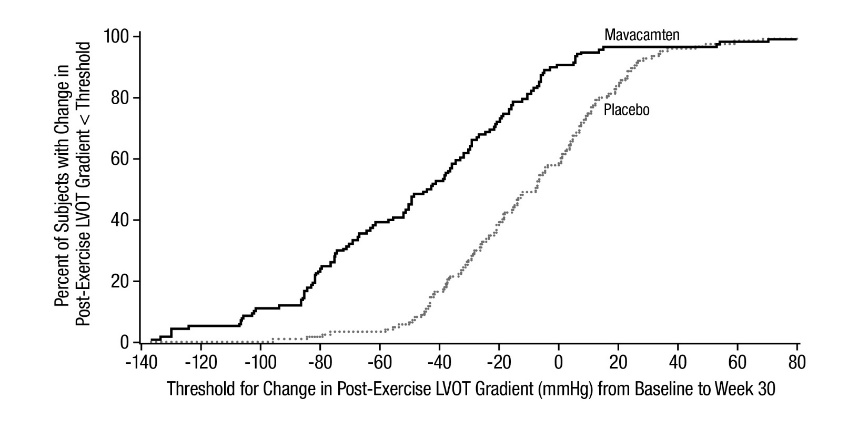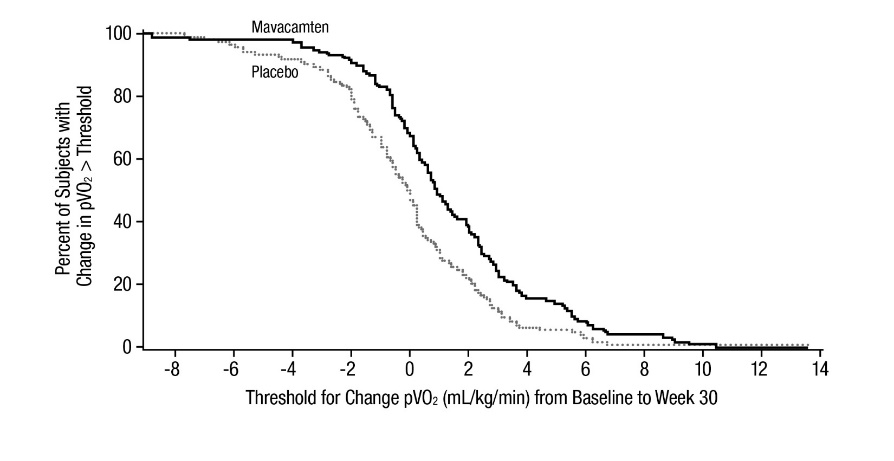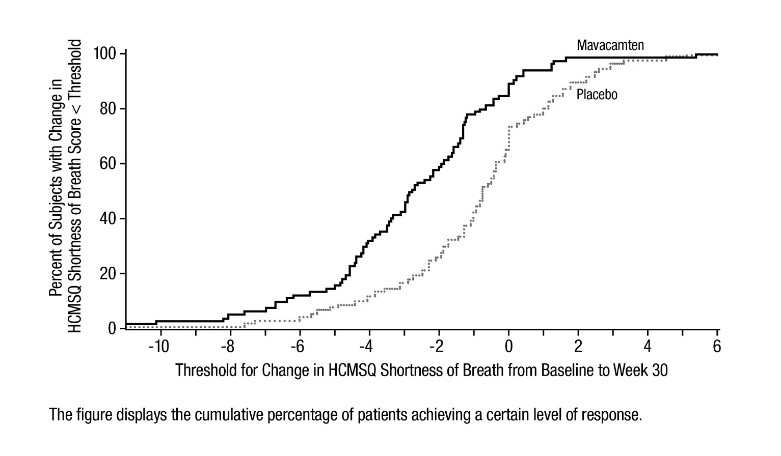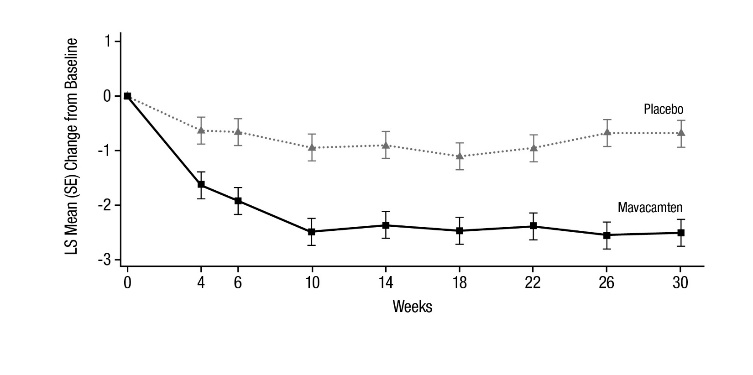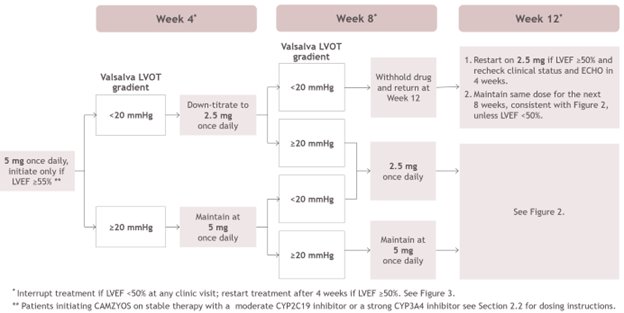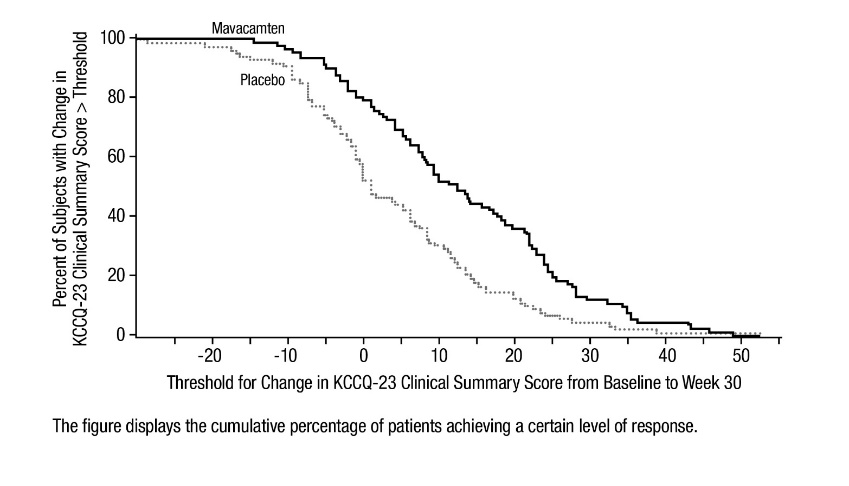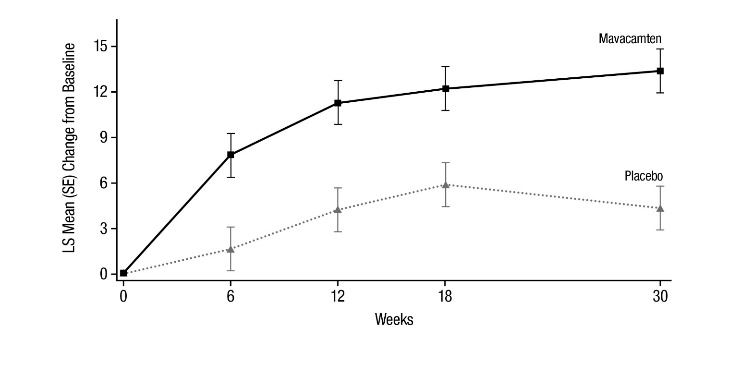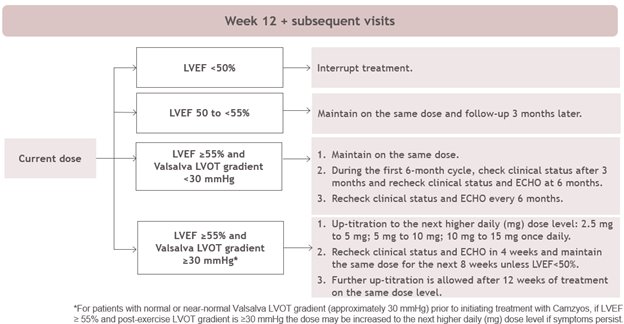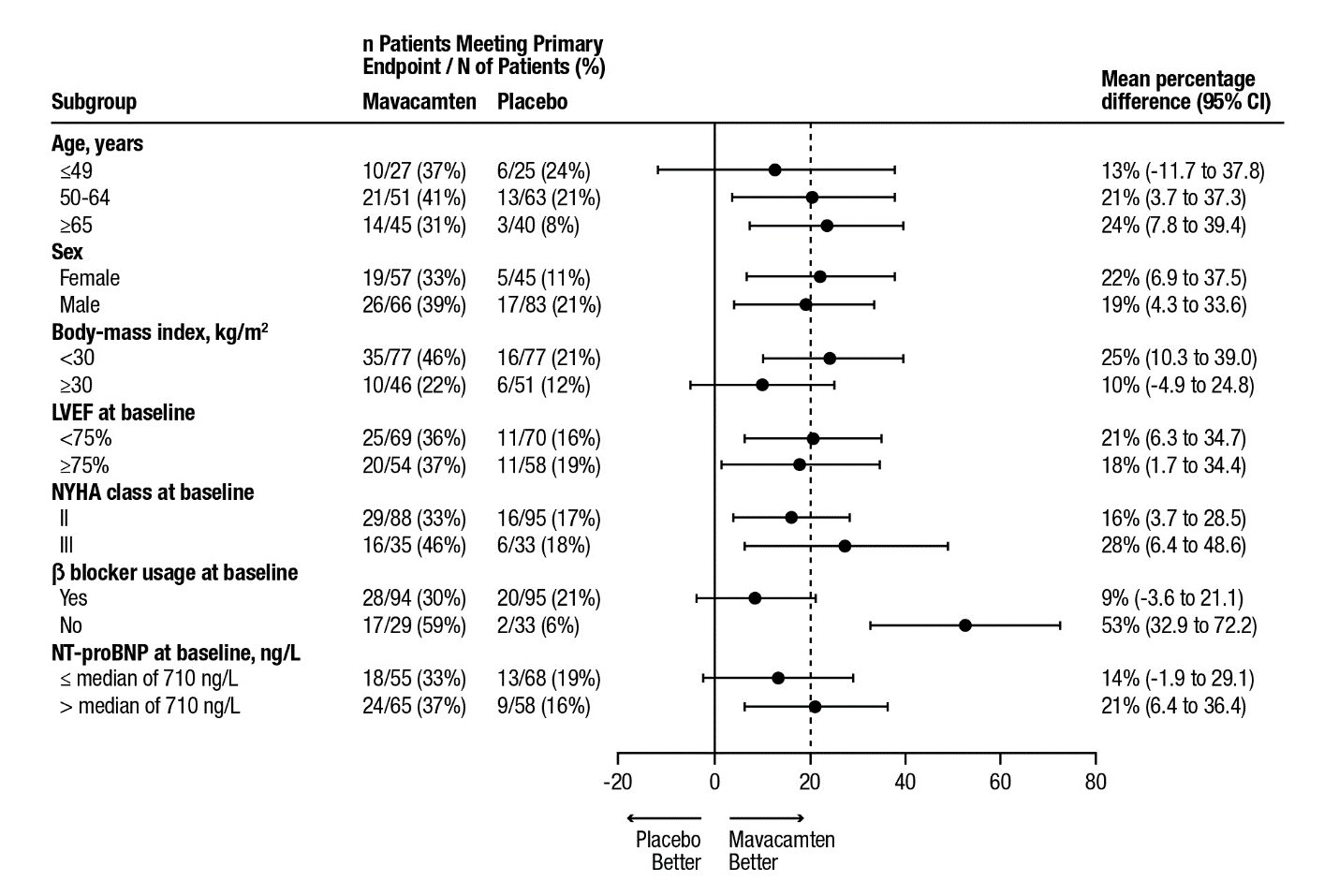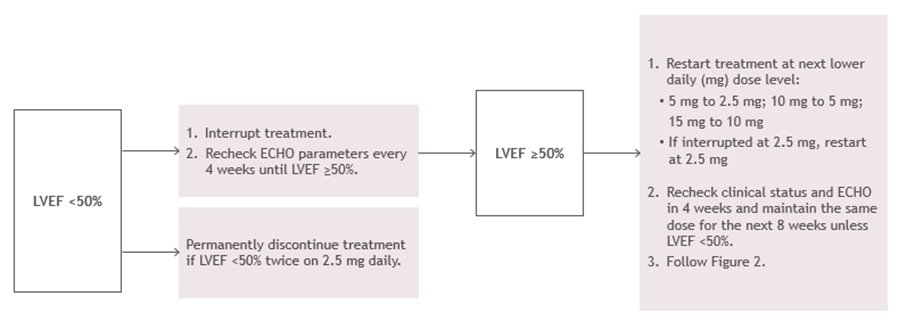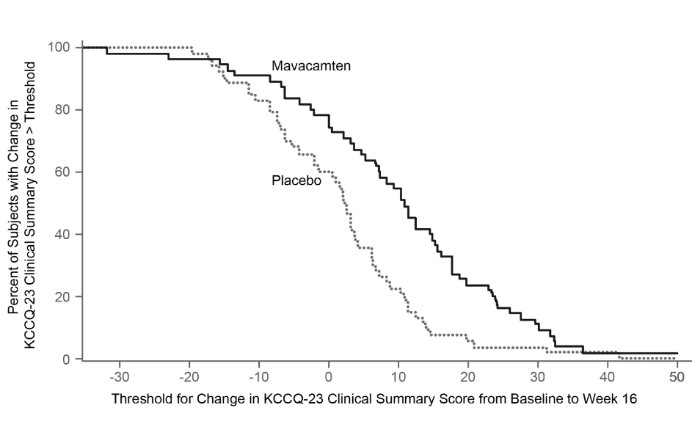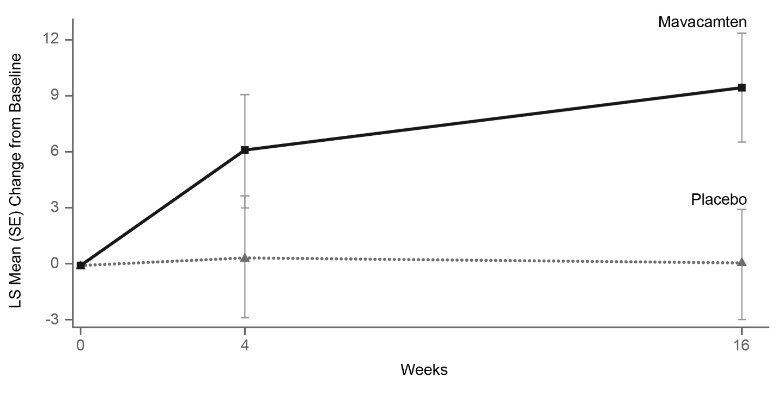 DRUG LABEL: CAMZYOS
NDC: 73625-111 | Form: CAPSULE, GELATIN COATED
Manufacturer: Myokardia, Inc.
Category: prescription | Type: HUMAN PRESCRIPTION DRUG LABEL
Date: 20250417

ACTIVE INGREDIENTS: MAVACAMTEN 2.5 mg/1 1
INACTIVE INGREDIENTS: CROSCARMELLOSE SODIUM; HYPROMELLOSE, UNSPECIFIED; MAGNESIUM STEARATE; MANNITOL; SILICON DIOXIDE; FERROSOFERRIC OXIDE; GELATIN, UNSPECIFIED; FERRIC OXIDE RED; TITANIUM DIOXIDE; FERRIC OXIDE YELLOW

HIGHLIGHTS OF PRESCRIBING INFORMATION

These highlights do not include all the information needed to use CAMZYOS safely and effectively. See full prescribing information for CAMZYOS.
CAMZYOS® (mavacamten) capsules for oral use
Initial U.S. Approval: 2022

RECENT MAJOR CHANGES

Boxed Warning | 04/2025
Dosage and Administration, Initiation, Maintenance, and Interruption of Treatment (2.1) | 04/2025
Dosage and Administration, Concomitant Administration of Weak to Moderate CYP2C19 or Moderate to Strong CYP3A4 Inhibitors (2.2) | 04/2025
Warnings and Precautions, Heart Failure (5.1) | 04/2025
Warnings and Precautions, Embryo-Fetal Toxicity (5.4) | 04/2025

WARNING: RISK OF HEART FAILURE

See full prescribing information for complete boxed warning.

- CAMZYOS can cause heart failure due to systolic dysfunction. (5.1)
- Echocardiogram assessments of left ventricular ejection fraction (LVEF) required before and during CAMZYOS use. (2.1)
- Initiation in patients with LVEF <55% not recommended.
Interrupt if LVEF <50% or if worsening clinical status. (2.1, 5.1)
- Certain CYP450 inhibitors and inducers are contraindicated in patients taking CAMZYOS because of an increased risk of heart failure. (4, 5.2, 7)
- CAMZYOS is available only through a restricted program called the CAMZYOS REMS Program. (5.3)

1 INDICATIONS AND USAGE

CAMZYOS is a cardiac myosin inhibitor indicated for the treatment of adults with symptomatic New York Heart Association (NYHA) class II-III obstructive hypertrophic cardiomyopathy (HCM) to improve functional capacity and symptoms. (1)

2 DOSAGE AND ADMINISTRATION

Dosage must be individualized based on clinical status and echocardiographic assessment of patient response. Refer to the Full Prescribing Information for instructions. (2.1)

3 DOSAGE FORMS AND STRENGTHS

Capsules: 2.5 mg, 5 mg, 10 mg, and 15 mg (3)

4 CONTRAINDICATIONS

- Strong CYP2C19 inhibitors. (4, 5.2)
- Moderate to strong CYP2C19 inducers or moderate to strong CYP3A4 inducers. (4, 5.2)

5 WARNINGS AND PRECAUTIONS

- Heart Failure: Consider interruption of CAMZYOS in patients with intercurrent illness. (2.1, 5.1)
- Drug Interactions Leading to Heart Failure or Loss of Effectiveness: Advise patients of the potential for drug interactions including with over-the-counter medications. (4, 5.2, 17)
- Embryo-Fetal Toxicity: May cause fetal harm. Advise females of reproductive potential to use effective contraception until 4 months after the last dose. Avoid concomitant use with a combined hormonal contraceptive that contains a progestin other than norethindrone. (5.4, 7.2, 8.1, 8.3)

6 ADVERSE REACTIONS

Adverse reactions occurring in >5% of patients and more commonly on CAMZYOS than on placebo were dizziness (27%) and syncope (6%). (6.1)

To report SUSPECTED ADVERSE REACTIONS, contact Bristol-Myers Squibb at 1-800-721-5072 or FDA at 1-800-FDA-1088 or www.fda.gov/medwatch.

7 DRUG INTERACTIONS

- Weak to moderate CYP2C19 inhibitors and moderate to strong CYP3A4 inhibitors: May increase risk of heart failure. If initiating an inhibitor, CAMZYOS dose reduction and additional monitoring are required. (2.2, 7.1)
- Negative inotropes: Close medical supervision and LVEF monitoring is recommended if a negative inotrope is initiated, or the dose of a negative inotrope is increased. Avoid certain combinations of negative inotropes. (7.3)

FULL PRESCRIBING INFORMATION

WARNING: RISK OF HEART FAILURE

CAMZYOS reduces left ventricular ejection fraction (LVEF) and can cause heart failure due to systolic dysfunction [see Warnings and Precautions (5.1)].

Echocardiogram assessments of LVEF are required prior to and during treatment with CAMZYOS. Initiation of CAMZYOS in patients with LVEF <55% is not recommended. Interrupt CAMZYOS if LVEF is <50% at any visit or if the patient experiences heart failure symptoms or worsening clinical status [see Dosage and Administration (2.1) and Warnings and Precautions (5.1)].

Concomitant use of CAMZYOS with certain cytochrome P450 inhibitors or discontinuation of certain cytochrome P450 inducers may increase the risk of heart failure due to systolic dysfunction; therefore, the use of CAMZYOS is contraindicated with the following [see Contraindications (4) and Warnings and Precautions (5.2)]:

- Strong CYP2C19 inhibitors
- Moderate to strong CYP2C19 inducers or moderate to strong CYP3A4 inducers

Because of the risk of heart failure due to systolic dysfunction, CAMZYOS is available only through a restricted program under a Risk Evaluation and Mitigation Strategy (REMS) called CAMZYOS REMS PROGRAM [see Warnings and Precautions (5.3)].

1 INDICATIONS AND USAGE

CAMZYOS® is indicated for the treatment of adults with symptomatic New York Heart Association (NYHA) class II-III obstructive hypertrophic cardiomyopathy (HCM) to improve functional capacity and symptoms.

2 DOSAGE AND ADMINISTRATION

2.1 Initiation, Maintenance, and Interruption of Treatment

Confirm absence of pregnancy and usage of effective contraception in females of reproductive potential [see Warnings and Precautions (5.4)].

Initiation or up-titration of CAMZYOS in patients with LVEF <55% is not recommended.

The recommended starting dose is 5 mg orally once daily without regard to food; allowable subsequent doses with titration are 2.5 mg, 5 mg, 10 mg, or 15 mg orally once daily. The maximum recommended dose is 15 mg orally once daily.

Patients may develop heart failure while taking CAMZYOS. Regular LVEF and Valsalva left ventricular outflow tract (LVOT) gradient assessment is required for careful titration to achieve an appropriate target Valsalva LVOT gradient, while maintaining LVEF ≥50% and avoiding heart failure symptoms (see Figure 1 and Figure 2).

Daily dosing takes weeks to reach steady-state drug levels and therapeutic effects, and genetic variation in metabolism and drug interactions can cause large differences in exposure [see Boxed Warning, Contraindications (4), Warnings and Precautions (5.2), Drug Interactions (7.1) and Clinical Pharmacology (12.3)].

When initiating or titrating CAMZYOS, first consider LVEF then consider the Valsalva LVOT gradient and patient clinical status to guide appropriate CAMZYOS dosing. Assessment of post-exercise LVOT gradient may be considered in symptomatic patients with normal or near normal Valsalva gradients (approximately 30 mmHg) prior to initiating treatment with CAMZYOS. Follow the algorithms for Initiation (Figure 1) and Maintenance (Figure 2) for appropriate CAMZYOS dosing and monitoring schedules.

If LVEF <50% while taking CAMZYOS, interrupt treatment. Follow the algorithm for Interruption (Figure 3) for guidance on interrupting, restarting, or discontinuing CAMZYOS. If interrupted at 2.5 mg, either restart at 2.5 mg or discontinue permanently.

Figure 1: Initiation Phase

Figure 2: Maintenance Phase

Figure 3: Treatment Interruption at Any Clinic Visit if LVEF <50%

Delay dose increases when there is intercurrent illness (e.g., serious infection) or arrhythmia (e.g., atrial fibrillation or other uncontrolled tachyarrhythmia) that may impair systolic function. Consider interruption of CAMZYOS in patients with intercurrent illness [see Warnings and Precautions (5.1)].

Missed or delayed doses

If a dose is missed, it should be taken as soon as possible, and the next scheduled dose should be taken at the usual time the following day. Exact timing of dosing during the day is not essential, but two doses should not be taken on the same day.

Swallow capsules whole. Do not break, open, or chew the capsules.

2.2 Concomitant Administration of Weak to Moderate CYP2C19 or Moderate to Strong CYP3A4 Inhibitors

Initiate CAMZYOS at the recommended starting dosage of 5 mg orally once daily in patients who are on stable therapy with a weak CYP2C19 inhibitor or a moderate CYP3A4 inhibitor (see Figure 1).

In patients who are on stable therapy with a moderate CYP2C19 inhibitor or a strong CYP3A4 inhibitor, initiate CAMZYOS at 2.5 mg orally once daily. Interrupt CAMZYOS treatment if Valsalva LVOT gradient is <20 mm Hg at Week 4 or Week 8. Treatment may be resumed after 4 weeks at 2.5 mg once daily if LVEF is ≥50%. If treatment is resumed at Week 12, recheck clinical status, Valsalva LVOT gradient and LVEF in 4 weeks, and maintain the current dose for the next 8 weeks unless LVEF is <50%.

In patients who initiate a weak to moderate CYP2C19 inhibitor or a moderate to strong CYP3A4 inhibitor, reduce dosage of CAMZYOS to the next lower daily (mg) dose level (i.e., 15 mg to 10 mg; 10 mg to 5 mg; or 5 mg to 2.5 mg). Schedule clinical and echocardiographic assessment 4 weeks after inhibitor initiation, and do not up-titrate to the next higher daily (mg) dose level of CAMZYOS until 12 weeks after inhibitor initiation. Avoid initiation of concomitant weak to moderate CYP2C19 and moderate to strong CYP3A4 inhibitors in patients who are on stable treatment with 2.5 mg of CAMZYOS because a lower CAMZYOS once-daily dose is not available [see Dosage and Administration (2.1), Drug Interactions (7.1)].

For short-term use (e.g., 1 week), interrupt CAMZYOS for the duration of treatment with a weak to moderate inhibitor of CYP2C19 or a moderate to strong inhibitor of CYP3A4. Mavacamten may be reinitiated at the previous dose immediately on discontinuation of concomitant therapy.

3 DOSAGE FORMS AND STRENGTHS

CAMZYOS is available as capsules imprinted with the strength and “Mava” in the following strengths:

- 2.5 mg – light purple cap
- 5 mg – yellow cap
- 10 mg – pink cap
- 15 mg – gray cap

4 CONTRAINDICATIONS

CAMZYOS is contraindicated with concomitant use of:

- Strong CYP2C19 inhibitors [see Warnings and Precautions (5.2), Drug Interactions (7.1)]
- Moderate to strong CYP2C19 inducers or moderate to strong CYP3A4 inducers [see Warnings and Precautions (5.2), Drug Interactions (7.1)]

5 WARNINGS AND PRECAUTIONS

5.1 Heart Failure

CAMZYOS reduces systolic contraction and can cause heart failure or significantly reduce ventricular function. Patients who experience a serious intercurrent illness (e.g., serious infection) or arrhythmia (e.g., atrial fibrillation or other uncontrolled tachyarrhythmia) are at greater risk of developing systolic dysfunction and heart failure [see Clinical Trial Experience (6.1)].

Assess the patient’s clinical status and LVEF prior to and regularly during treatment and adjust the CAMZYOS dose accordingly [see Dosage and Administration (2.1)]. New or worsening arrhythmia, dyspnea, chest pain, fatigue, palpitations, leg edema, or elevations in N-terminal pro-B-type natriuretic peptide (NT-proBNP) may be signs and symptoms of heart failure and should also prompt an evaluation of cardiac function.

Asymptomatic LVEF reduction, intercurrent illnesses, and arrhythmias require additional dosing considerations [see Dosage and Administration (2.1, 2.2)].

Initiation of CAMZYOS in patients with LVEF <55% is not recommended. Avoid concomitant use of CAMZYOS in patients on disopyramide, ranolazine, verapamil with a beta blocker, or diltiazem with a beta blocker as these medications and combinations increase the risk of left ventricular systolic dysfunction and heart failure symptoms and clinical experience is limited [see Drug Interactions (7)].

5.2 CYP450 Drug Interactions Leading to Heart Failure or Loss of Effectiveness

CAMZYOS is primarily metabolized by CYP2C19 and CYP3A4 enzymes. Concomitant use of CAMZYOS and drugs that interact with these enzymes may lead to life-threatening drug interactions such as heart failure or loss of effectiveness [see Contraindications (4), Warnings and Precautions (5.1), and Drug Interactions (7.1)].

Advise patients of the potential for drug interactions, including with over-the-counter medications (such as omeprazole, esomeprazole, or cimetidine). Advise patients to inform their healthcare provider of all concomitant products prior to and during CAMZYOS treatment [see Drug Interactions (7.1), Patient Counseling Information (17)].

5.3 CAMZYOS REMS Program

CAMZYOS is only available through a restricted program called the CAMZYOS REMS Program because of the risk of heart failure due to systolic dysfunction [see Warnings and Precautions (5.1, 5.2)].

Notable requirements of the CAMZYOS REMS Program include the following:

- Prescribers must be certified by enrolling in the CAMZYOS REMS Program.
- Patients must enroll in the CAMZYOS REMS Program and comply with ongoing monitoring requirements [see Dosage and Administration (2.1)].
- Pharmacies must be certified by enrolling in the CAMZYOS REMS Program and must only dispense to patients who are authorized to receive CAMZYOS.
- Wholesalers and distributors must only distribute to certified pharmacies.

Further information is available at www.CAMZYOSREMS.com or by telephone at 1-833-628-7367.

5.4 Embryo-Fetal Toxicity

CAMZYOS may cause fetal toxicity when administered to a pregnant female, based on findings in animal studies. Confirm absence of pregnancy in females of reproductive potential prior to treatment and advise patients to use effective contraception during treatment with CAMZYOS and for 4 months after the last dose. Combined hormonal contraceptives (CHCs) containing a combination of ethinyl estradiol and norethindrone may be used with mavacamten. However, CAMZYOS may reduce the effectiveness of certain other CHCs. If these CHCs are used, advise patients to add nonhormonal contraception (such as condoms) during concomitant use and for 4 months after the last dose of CAMZYOS [see Drug Interactions (7.2) and Use in Specific Populations (8.1, 8.3)].

6 ADVERSE REACTIONS

The following adverse reaction is discussed in other sections of the labeling:

- Heart failure [see Warnings and Precautions (5.1)]

6.1 Clinical Trials Experience

Because clinical trials are conducted under widely varying conditions, adverse reaction rates observed in the clinical trials of a drug cannot be directly compared to rates in the clinical trials of another drug and may not reflect the rates observed in practice.

The safety of CAMZYOS was evaluated in EXPLORER-HCM, a Phase 3, double-blind, randomized, placebo-controlled trial [see Clinical Studies (14)]. Of the 251 adults with obstructive HCM, 123 patients were treated with CAMZYOS 2.5-15 mg daily and 128 were treated with placebo. CAMZYOS-treated patients had a median duration of exposure of 30 weeks (range: 2-40 weeks).

Syncope (0.8%) was the only adverse drug reaction leading to discontinuation in patients receiving CAMZYOS.

Adverse reactions occurring in >5% of patients and more commonly on CAMZYOS than on placebo were dizziness (27% vs. 18%) and syncope (6% vs. 2%).

The safety of CAMZYOS in patients was further evaluated in VALOR-HCM, a Phase 3, double-blind, randomized, placebo-controlled trial [see Clinical Studies (14)]. Of the 112 adults with symptomatic obstructive HCM, 56 patients were treated with CAMZYOS 2.5-15 mg daily and 55 were treated with placebo. CAMZYOS-treated patients had a median duration of exposure of 17 weeks (range: 3-19 weeks).

There were no new adverse reactions identified in VALOR-HCM.

Effects on Systolic Function

In the EXPLORER-HCM trial, mean (SD) resting LVEF was 74% (6) at baseline in both treatment groups. Consistent with the mechanism of action of CAMZYOS, mean (SD) absolute change from baseline in LVEF was -4% (8) in the CAMZYOS group and 0% (7) in the placebo group over the 30-week treatment period. At Week 38, following an 8-week interruption of trial drug, mean LVEF was similar to baseline for both treatment groups. In the EXPLORER-HCM trial, 7 (6%) patients in the CAMZYOS group and 2 (2%) patients in the placebo group experienced reversible reductions in LVEF to <50% (median 48%: range 35-49%) while on treatment. In 3 of the 7 CAMZYOS patients and 1 of the 2 placebo patients, these reductions were asymptomatic. In all 7 patients treated with CAMZYOS, LVEF recovered following interruption of CAMZYOS [see Warnings and Precautions (5.1)].

7 DRUG INTERACTIONS

7.1 Potential for Other Drugs to Affect Plasma Concentrations of CAMZYOS

Mavacamten is primarily metabolized by CYP2C19 and to a lesser extent by CYP3A4 and CYP2C9. Inducers and inhibitors of CYP2C19 and moderate to strong inhibitors or inducers of CYP3A4 may affect the exposures of mavacamten [see Warnings and Precautions (5.2) and Clinical Pharmacology (12.3)]. (See Table 1)

Table 1: Established and Potentially Significant Pharmacokinetic Drug Interactions with CAMZYOS

Impact of Other Drugs on CAMZYOS

Strong CYP2C19 Inhibitors
Clinical Impact | Concomitant use with a strong CYP2C19 inhibitor increases mavacamten exposure, which may increase the risk of heart failure due to systolic dysfunction [see Contraindications (4), Warnings and Precautions (5.2), Clinical Pharmacology (12.3)].
Prevention or Management | Concomitant use with a strong CYP2C19 inhibitor is contraindicated.
Moderate to Strong CYP2C19 Inducers or Moderate to Strong CYP3A4 Inducers
Clinical Impact | Concomitant use with a moderate to strong CYP2C19 inducer or a moderate to strong CYP3A4 inducer decreases mavacamten exposure, which may reduce CAMZYOS’ efficacy [see Clinical Pharmacology (12.3)]. The risk of heart failure due to systolic dysfunction may increase with discontinuation of these inducers as the levels of induced enzyme normalizes [see Contraindications (4) and Warnings and Precautions (5.2)].
Prevention or Management | Concomitant use of a moderate to strong CYP2C19 inducer or a moderate to strong CYP3A4 inducer is contraindicated.
Weak CYP2C19 Inhibitors or Moderate CYP3A4 Inhibitors
Clinical Impact | Concomitant use with a weak CYP2C19 inhibitor or a moderate CYP3A4 inhibitor increases mavacamten exposure, which may increase the risk of adverse drug reactions [see Warnings and Precautions (5.2)].
Prevention or Management | Initiate CAMZYOS at the recommended starting dosage of 5 mg orally once daily in patients who are on stable therapy with a weak CYP2C19 inhibitor or a moderate CYP3A4 inhibitor.; Reduce dose of CAMZYOS to the next lower daily (mg) dose level (i.e., 15 mg to 10 mg, 10 mg to 5 mg, or 5 mg to 2.5 mg) in patients who are on CAMZYOS treatment and intend to initiate a weak CYP2C19 inhibitor or a moderate CYP3A4 inhibitor. Avoid initiation of concomitant weak CYP2C19 and moderate CYP3A4 inhibitors in patients who are on stable treatment with 2.5 mg of CAMZYOS because a lower dose is not available [see Dosage and Administration (2.2)].; For short-term use (e.g., 1 week), interrupt CAMZYOS for the duration of treatment with a weak inhibitor of CYP2C19 or a moderate inhibitor of CYP3A4. CAMZYOS may be reinitiated at the previous dose immediately on discontinuation of concomitant therapy.
Moderate CYP2C19 Inhibitors or Strong CYP3A4 Inhibitors
Clinical Impact | Concomitant use with a moderate CYP2C19 inhibitor or a strong CYP3A4 inhibitor increases mavacamten exposure, which may increase the risk of adverse drug reactions [see Warnings and Precautions (5.2)]. Discontinuing use of a moderate CYP2C19 inhibitor or strong CYP3A4 inhibitor after long-term concomitant use may decrease mavacamten exposure, which may reduce CAMZYOS’ efficacy [see Clinical Pharmacology (12.3)].
Prevention or Management | Initiate CAMZYOS at a starting dosage of 2.5 mg orally once daily in patients who are on stable therapy with a moderate CYP2C19 inhibitor or a strong CYP3A4 inhibitor.; Reduce dose of CAMZYOS to the next lower daily (mg) dose level (i.e., 15 mg to 10 mg, 10 mg to 5 mg, or 5 mg to 2.5 mg) in patients who are on CAMZYOS and intend to initiate a moderate CYP2C19 inhibitor or a strong CYP3A4 inhibitor. Avoid initiation of concomitant moderate CYP2C19 and strong CYP3A4 inhibitors in patients who are on stable treatment with 2.5 mg of CAMZYOS because a lower dose is not available [see Dosage and Administration (2.2)].; An increase in dose of CAMZYOS may be needed if the moderate inhibitor of CYP2C19 or strong inhibitor of CYP3A4 is discontinued after long-term concomitant use. Monitor for new or worsening symptoms.; For short-term use (e.g., 1 week), interrupt CAMZYOS for the duration of treatment with a moderate inhibitor of CYP2C19 or a strong inhibitor of CYP3A4. CAMZYOS may be reinitiated at the previous dose immediately on discontinuation of concomitant therapy.

7.2 Potential for CAMZYOS to Affect Plasma Concentrations of Other Drugs

Certain CYP3A4, CYP2C9, and CYP2C19 Substrates

Mavacamten is an inducer of CYP3A4, CYP2C9, and CYP2C19. Concomitant use with CYP3A4, CYP2C9, or CYP2C19 substrates may reduce plasma concentration of these drugs [see Clinical Pharmacology (12.3)]. Closely monitor when CAMZYOS is used with concomitant CYP3A4, CYP2C9 or CYP2C19 substrates unless otherwise recommended in the Prescribing Information.

Certain Combined Hormonal Contraceptives

Progestin and ethinyl estradiol are CYP3A4 substrates. Concomitant use of CAMZYOS may decrease exposures of certain progestins [see Clinical Pharmacology (12.3)], which may lead to contraceptive failure. Combined hormonal contraceptives (CHCs) containing a combination of ethinyl estradiol and norethindrone may be used with mavacamten, but if other CHCs are used, advise patients to add nonhormonal contraception (such as condoms) or use an alternative contraceptive method that is not affected by CYP450 enzyme induction (e.g., intrauterine system) during concomitant use and for 4 months after the last dose of CAMZYOS.

7.3 Drugs That Reduce Cardiac Contractility

Expect additive negative inotropic effects of CAMZYOS and other drugs that reduce cardiac contractility. Avoid concomitant use of CAMZYOS in patients on disopyramide, ranolazine, verapamil with a beta blocker, or diltiazem with a beta blocker as these medications and combinations increase the risk of left ventricular systolic dysfunction and heart failure symptoms and clinical experience is limited [see Warnings and Precautions (5.1)].

If concomitant therapy with a negative inotrope is initiated, or if the dose of a negative inotrope is increased, monitor LVEF closely until stable doses and clinical response have been achieved.

8 USE IN SPECIFIC POPULATIONS

8.1 Pregnancy

Risk Summary

Based on animal data, CAMZYOS may cause fetal harm when administered to a pregnant female. There are no human data on the use of CAMZYOS during pregnancy to evaluate for a drug-associated risk of major birth defects, miscarriage, or other adverse maternal or fetal outcomes. The underlying maternal condition during pregnancy poses a risk to the mother and fetus (see Clinical Considerations). Advise pregnant females about the potential risk to the fetus with maternal exposure to CAMZYOS during pregnancy.

In animal embryo-fetal development studies, mavacamten-related decreases in mean fetal body weight, reductions in fetal ossification of bones, and increases in post-implantation loss (early and/or late resorptions) were observed in rats and increases in visceral and skeletal malformations were observed in both rabbits and rats at dose exposures similar to that achieved at the maximum recommended human dose (MRHD) (see Data).

The estimated background risk of major birth defects and miscarriage for the indicated population is unknown. All pregnancies have a background risk of birth defect, loss, or other adverse outcomes. In the U.S. general population, the estimated background risk of major birth defects and miscarriage in clinically recognized pregnancies is 2% to 4% and 15% to 20%, respectively.

There is a pregnancy safety study for CAMZYOS. If CAMZYOS is administered during pregnancy, or if a patient becomes pregnant while receiving CAMZYOS or within 4 months after the last dose of CAMZYOS, healthcare providers should report CAMZYOS exposure by contacting Bristol-Myers Squibb at 1-800-721-5072 or www.bms.com.

Clinical Considerations

Disease-Associated Maternal and Embryo-Fetal Risk

Obstructive HCM in pregnancy has been associated with increased risk for preterm birth.

Data

Animal Data

When mavacamten was administered orally to pregnant rats (0.3 to 1.5 mg/kg/day) during the period of organogenesis, increases in post-implantation loss, decreases in mean fetal body weight, reductions in fetal ossification of bones, and fetal malformations (visceral and skeletal) were observed in the high dose group (1.5 mg/kg/day). Visceral malformations (heart malformation in fetuses, including one total situs inversus) and increased incidences of skeletal malformations (mainly fused sternebrae) were observed at a similar exposure as in humans at the MRHD. Plasma exposure (based on area under the concentration-time curve or AUC) at the no-effect dose for embryo-fetal development in rats is 0.3 times the exposure in humans at the MRHD.

When mavacamten was administered orally to pregnant rabbits (0.6 to 2.0 mg/kg/day) during the period of organogenesis, fetal malformations (visceral and skeletal) were increased at doses of 1.2 mg/kg/day and higher, with similar plasma exposure at 1.2 mg/kg/day as in humans at the MRHD. Visceral findings consisted of malformations of the great vessels (dilatation of pulmonary trunk and/or aortic arch). Skeletal malformations consisted of higher incidences of fused sternebrae at ≥1.2 mg/kg/day. Plasma exposure (AUC) at the no-effect dose for embryo-fetal development in rabbits is 0.4 times the exposure in humans at the MRHD.

In a pre/postnatal development study, mavacamten was administered orally to pregnant rats (0.3, to 1.5 mg/kg/day) from gestation Day 6 to lactation/post-partum Day 20. No adverse effects were observed in the dams or offspring exposed daily from before birth (in utero) through lactation. The no-observed-adverse-effect level (NOAEL) was 1.5 mg/kg/day (the highest dosage level tested), with similar exposure (AUC) as in humans at the MRHD.

8.2 Lactation

Risk Summary

The presence of mavacamten in human or animal milk, the drug’s effects on the breastfed infant, and the effects on milk production are unknown. The developmental and health benefits of breastfeeding should be considered along with the mother’s clinical need for CAMZYOS and any potential adverse effects on the breastfed child from CAMZYOS or from the underlying maternal condition.

8.3 Females and Males of Reproductive Potential

Based on animal data, CAMZYOS may cause fetal harm when administered to a pregnant female [see Warnings and Precautions (5.4) and Use in Specific Populations (8.1)].

Pregnancy Testing

Confirm absence of pregnancy in females of reproductive potential prior to initiation of CAMZYOS.

Contraception

Females

Advise females of reproductive potential to use effective contraception during treatment with CAMZYOS and for 4 months after the last dose. CHCs containing a combination of ethinyl estradiol and norethindrone may be used with CAMZYOS. However, CAMZYOS may reduce the effectiveness of certain other CHCs. If these CHCs are used, advise patients to add nonhormonal contraception (such as condoms) or use an alternative contraceptive method during concomitant use and for 4 months after the last dose of CAMZYOS [see Drug Interactions (7.2)].

8.4 Pediatric Use

The safety and effectiveness of CAMZYOS have not been established in pediatric patients.

8.5 Geriatric Use

Clinical trials included 319 patients dosed with CAMZYOS, 119 of whom were 65 years of age or older (37.3%), and 25 of whom (7.8%) were age 75 years or older. Safety, effectiveness, and pharmacokinetics were similar between patients ≥65 years and younger patients.

8.6 Hepatic Impairment

No dosage adjustment is required in patients with mild (Child-Pugh A) to moderate (Child-Pugh B) hepatic impairment. Mavacamten exposure (AUC) increased up to 220% in patients with mild (Child-Pugh A) or moderate (Child-Pugh B) hepatic impairment compared to patients with normal hepatic function. However, no additional dose adjustment is required in patients with mild to moderate hepatic impairment with the recommended dose titration algorithm and monitoring plan. The effect of severe (Child-Pugh C) hepatic impairment is unknown [see Clinical Pharmacology (12.3)].

10 OVERDOSAGE

Clinical Experience and Effects

- Cardiovascular effects may include reduced LVEF (left ventricular ejection fraction), heart failure, hypotension, and asystole refractory to medical intervention.
- Neurological effects may include dizziness and syncope.
- An infant death was reported after accidental ingestion of three 15 mg capsules (45 mg).
- An adult administered a single dose of 144 mg developed a vasovagal reaction, hypotension, and asystole, but the subject recovered.

Management

- Discontinue CAMZYOS treatment.
- Provide medically supportive measures to maintain hemodynamic stability and monitor left ventricular function.
- Consider administering activated charcoal (pediatric dose is 1 g/kg; adult dose is 50 g) within 2 hours of ingestion in addition to other supportive measures. The benefit of activated charcoal is negligible after 6 hours [see Clinical Pharmacology (12.3)].
- Consider contacting the Poison Help line (1-800-222-1222) or a medical toxicologist for additional overdose management recommendations.

11 DESCRIPTION

CAMZYOS capsules for oral use contain mavacamten, a cardiac myosin inhibitor.

The chemical name of mavacamten is 3-(1-methylethyl)-6-[[(1S)-1-phenylethyl]amino]-2,4(1H,3H)-pyrimidinedione. The molecular formula is C15H19N3O2, and the molecular weight is 273.33 g/mol.

The structural formula of mavacamten is:

Mavacamten is a white to off-white powder that is practically insoluble in water and aqueous buffers at pH 2-10, sparingly soluble in methanol and ethanol, and freely soluble in DMSO and NMP.

CAMZYOS is supplied as immediate release Size 2 hard gelatin capsules, containing 2.5 mg, 5 mg, 10 mg, or 15 mg of mavacamten per capsule as active ingredient and the following inactive ingredients: croscarmellose sodium, hypromellose, magnesium stearate (non-bovine), mannitol, and silicon dioxide. The capsule shell contains black edible ink, black iron oxide, gelatin, red iron oxide, titanium dioxide, and yellow iron oxide.

12 CLINICAL PHARMACOLOGY

12.1 Mechanism of Action

Mavacamten is an allosteric and reversible inhibitor selective for cardiac myosin. Mavacamten modulates the number of myosin heads that can enter “on actin” (power-generating) states, thus reducing the probability of force-producing (systolic) and residual (diastolic) cross-bridge formation. Excess myosin actin cross-bridge formation and dysregulation of the super-relaxed state are mechanistic hallmarks of HCM. Mavacamten shifts the overall myosin population towards an energy-sparing, recruitable, super-relaxed state. In HCM patients, myosin inhibition with mavacamten reduces dynamic LVOT obstruction and improves cardiac filling pressures.

12.2 Pharmacodynamics

Left Ventricular Ejection Fraction and Left Ventricular Outflow Tract Obstruction

In the EXPLORER-HCM trial, patients achieved reductions in mean resting and provoked (Valsalva) LVOT gradient by Week 4 which were sustained throughout the 30-week trial. At Week 30, the mean (SD) changes from baseline in resting and Valsalva LVOT gradients were -39 (29) mmHg and -49 (34) mmHg, respectively, for the CAMZYOS group and -6 (28) mmHg and -12 (31) mmHg, respectively, for the placebo group. The reductions in Valsalva LVOT gradient were accompanied by decreases in LVEF, generally within the normal range. Eight weeks after discontinuation of CAMZYOS, mean LVEF and Valsalva LVOT gradients were similar to baseline.

Cardiac Structure

In EXPLORER-HCM, echocardiographic measurements of cardiac structure showed a mean (SD) reduction from baseline at Week 30 in left ventricular mass index (LVMI) in the mavacamten group (-7.4 [17.8] g/m^2) versus an increase in LVMI in the placebo group (8.9 [15.3] g/m^2). There was also a mean (SD) reduction from baseline in left atrial volume index (LAVI) in the mavacamten group (-7.5 [7.8] mL/m^2) versus no change in the placebo group (-0.1 [8.7] mL/m^2). The clinical significance of these findings is unknown.

Cardiac Biomarkers

In the EXPLORER-HCM trial [see Clinical Studies (14)], reductions in a biomarker of cardiac wall stress, NT-proBNP, were observed by Week 4 and sustained through the end of treatment. At Week 30 compared with baseline, the reduction in NT-proBNP after mavacamten treatment was 80% greater than for placebo (proportion of geometric mean ratio between the two groups, 0.20 [95% CI: 0.17, 0.24]).

In the VALOR-HCM trial [see Clinical Studies (14)], a reduction in NT-proBNP was observed by Week 8 and sustained throughout treatment. At Week 16 compared with baseline, the reduction in NT-proBNP after mavacamten treatment was 67% greater than for placebo (proportion of geometric mean ratio between the two groups, 0.33 [95% CI: 0.27, 0.42]). At Week 16 compared with baseline, a reduction in cardiac troponin I after mavacamten treatment was 47% greater than for placebo (proportion of geometric mean ratio between the two groups, 0.53 [95% CI: 0.41, 0.70]).

The clinical significance of the NT-proBNP and troponin findings is unknown.

Cardiac Electrophysiology

In healthy volunteers receiving multiple doses of CAMZYOS, a concentration-dependent increase in the QTc interval was observed at doses up to 25 mg once daily. No acute QTc changes have been observed at similar exposures during single-dose studies. The mechanism of the QT prolongation effect is not known.

A meta-analysis across clinical studies in HCM patients does not suggest clinically relevant increases in the QTc interval in the therapeutic exposure range. In HCM, the QT interval may be intrinsically prolonged due to the underlying disease, in association with ventricular pacing, or in association with drugs with potential for QT prolongation commonly used in the HCM population. The effect of coadministration of CAMZYOS with other QT-prolonging drugs or in patients with potassium channel variants resulting in a long QT interval have not been characterized.

12.3 Pharmacokinetics

Mavacamten exposure increases dose proportionally following multiple once-daily doses of 1 mg to 15 mg. At the same dose level of CAMZYOS, 170% higher exposures of mavacamten are observed in patients with HCM compared to healthy subjects. Mavacamten accumulation is approximately 100% for Cmax and approximately 600% for AUC in CYP2C19 normal metabolizers (NMs). The accumulation is dependent upon the CYP2C19 metabolism status with the largest accumulation occurring in CYP2C19 poor metabolizers (PMs). At steady-state, the peak-to-trough mavacamten plasma concentration ratio with once daily dosing is approximately 1.5.

Absorption

Mavacamten has an estimated oral bioavailability of at least 85% and median time to maximum concentration (Tmax) of 1 to 2 hours.

Effect of Food

No clinically significant differences in mavacamten AUC were observed following its administration with a high fat meal.

Distribution

Plasma protein binding of mavacamten is between 97 and 98%.

Elimination

Mavacamten has a variable terminal t1/2 that depends on CYP2C19 metabolic status. Mavacamten terminal half‑life is 6 to 9 days in CYP2C19 normal metabolizers (NMs), which is prolonged in CYP2C19 poor metabolizers (PMs) to 23 days.

Metabolism

Mavacamten is extensively metabolized, primarily through CYP2C19 (74%), CYP3A4 (18%), and CYP2C9 (8%).

Excretion

Following a single 25-mg dose of radiolabeled mavacamten, 7% of the dose was recovered in feces (1% unchanged) and 85% in urine (3% unchanged).

Specific Populations

No clinically significant differences in the pharmacokinetics of mavacamten were observed based on age (range: 18-82 years), sex, race, ethnicity, or mild (eGFR: 60 to 89 mL/min/1.73 m^2) to moderate (eGFR: 30 to 59 mL/min/1.73 m^2) renal impairment. The effects of severe (eGFR: 15 to 30 mL/min/1.73 m^2) renal impairment and kidney failure (eGFR: <15 mL/min/1.73 m^2; including patients on dialysis) are unknown.

Hepatic Impairment

Mavacamten exposures (AUC) increased up to 220% in patients with mild (Child-Pugh A) or moderate (Child-Pugh B) hepatic impairment. The effect of severe (Child-Pugh C) hepatic impairment is unknown.

Drug Interactions

Clinical Studies and Model-Informed Approaches

Weak CYP2C19 Inhibitors: Concomitant use of mavacamten (15 mg) with omeprazole (20 mg) once daily increased mavacamten AUCinf by 48% with no effect on Cmax in healthy CYP2C19 NMs and rapid metabolizers (RMs; e.g., *1/*17).

Moderate CYP3A4 Inhibitors: Concomitant use of mavacamten (25 mg) with verapamil sustained release (240 mg) increased mavacamten AUCinf by 16% and Cmax by 52% in intermediate metabolizers (IMs; e.g., *1/*2, *1/*3, *2/*17, *3/*17) and NMs of CYP2C19. Concomitant use of mavacamten with diltiazem in CYP2C19 PMs is predicted to increase mavacamten AUC0-24h and Cmax up to 55% and 42%, respectively.

Strong CYP3A4 Inhibitors: Concomitant use of mavacamten (15 mg) with ketoconazole 400 mg once daily in CYP2C19 poor metabolizers is predicted to increase mavacamten AUC0-24 and Cmax up to 130% and 90%, respectively.

Strong CYP2C19 and CYP3A4 Inducers: Concomitant use of mavacamten (a single 15-mg dose) with a strong CYP2C19 and CYP3A4 inducer (rifampin 600-mg daily dose) is predicted to decrease mavacamten AUC0-inf and Cmax by 87% and 22%, respectively, in CYP2C19 NMs, and by 69% and 4%, respectively, in CYP2C19 PMs.

CYP3A4 Substrates: Concomitant use of a 16‑day course of mavacamten (25 mg on Days 1 and 2, followed by 15 mg for 14 days) decreased AUCinf and Cmax of midazolam by 13% and 7%, respectively, in healthy subjects. Following coadministration of mavacamten once daily in HCM patients at the upper end of the therapeutic range, midazolam AUCinf and Cmax are predicted to decrease up to 45% and 24%, respectively.

Certain combined oral contraceptives: No clinically significant differences in ethinyl estradiol and norethindrone exposure were observed in healthy female subjects with CYP2C19 NM phenotype following concomitant use of a combined oral contraceptive containing ethinyl estradiol and norethindrone with a 17-day course of mavacamten (25 mg on days 1 and 2, followed by 15 mg for 15 days). The impact of mavacamten on oral contraceptives containing other progestins is unknown.

CYP2C8 Substrates: Concomitant use of mavacamten once daily in HCM patients is predicted to decrease AUC and Cmax of repaglinide, a CYP2C8 and CYP3A substrate, by up to 27% and 19%, respectively, depending on the dose of mavacamten and CYP2C19 phenotype.

CYP2C9 Substrates: Concomitant use of mavacamten once daily in HCM patients is predicted to decrease AUC and Cmax of tolbutamide, a CYP2C9 substrate, by up to 54% and 23%, respectively, depending on the dose of mavacamten and CYP2C19 phenotype.

CYP2C19 Substrates: Concomitant use of mavacamten once daily in HCM patients is predicted to decrease AUC and Cmax of omeprazole, a CYP2C19 substrate, by up to 48% and 17%, respectively, depending on the dose of mavacamten and CYP2C19 phenotype.

Activated Charcoal: Mavacamten AUC0-72h and AUC0-infinity was reduced by 14% and 34%, respectively, following administration of 50 g activated charcoal with sorbitol 2 hours after ingestion of a single mavacamten 15 mg dose. Administration of activated charcoal 6 hours after the mavacamten dose had minimal effect on mavacamten exposure.

In Vitro Studies

CYP Enzymes: Mavacamten does not inhibit CYP1A2, CYP2B6, CYP2C8, CYP2D6, CYP2C9, CYP2C19, or CYP3A4. Mavacamten is a CYP2B6 inducer.

Transporter Systems: Mavacamten does not inhibit P-gp, BCRP, BSEP, MATE1, MATE2-K, organic anion transporting polypeptides (OATPs), organic cation transporters (OCTs), or organic anion transporters (OATs).

12.5 Pharmacogenomics

Mavacamten AUCinf increased by 241% and Cmax increased by 47% in CYP2C19 poor metabolizers (PMs) compared to normal metabolizers (NMs) following a single dose of 15 mg mavacamten. Mean half-life is prolonged in CYP2C19 PMs compared to NMs (23 days vs. 6 to 9 days, respectively).

Polymorphic CYP2C19 is the main enzyme involved in the metabolism of CAMZYOS. An individual carrying two normal function alleles is a NM (e.g., *1/*1). An individual carrying two no function alleles is a PM (e.g., *2/*2, *2/*3, *3/*3).

The prevalence of CYP2C19 poor metabolizers differs depending on ancestry. Approximately 2% of individuals of European ancestry and 4% of individuals of African ancestry are PMs; the prevalence of PMs is higher in Asian populations (e.g., approximately 13% of East Asians).

13 NONCLINICAL TOXICOLOGY

13.1 Carcinogenesis, Mutagenesis, and Impairment of Fertility

Mavacamten was not genotoxic in a bacterial reverse mutation test (Ames test), a human in vitro lymphocyte clastogenicity assay, or a rat in vivo micronucleus assay.

There was no evidence of carcinogenicity seen in a 6-month rasH2 transgenic mouse study at mavacamten doses of up to 2.0 mg/kg/day in males and 3.0 mg/kg/day in females, or in a 2-year rat study at mavacamten doses up to 0.6 mg/kg/day. The exposure-based (AUC) safety margins in mice and rats were up to 3X or 0.2X, respectively, compared to AUC exposures in humans at the MRHD.

In reproductive toxicity studies, there was no evidence of effects of mavacamten on mating and fertility in male or female rats at doses up to 1.2 mg/kg/day, or on the viability and fertility of offspring of dams dosed up to 1.5 mg/kg/day. Plasma exposure (AUC) of mavacamten at the highest dose tested was the same as in humans at the MRHD.

14 CLINICAL STUDIES

EXPLORER-HCM

The efficacy of CAMZYOS was evaluated in EXPLORER-HCM (NCT-03470545) a Phase 3, double-blind, randomized, placebo-controlled, multicenter, international, parallel-group trial in 251 adults with symptomatic NYHA class II and III obstructive HCM, LVEF ≥55%, and LVOT peak gradient ≥50 mmHg at rest or with provocation.

Patients on dual therapy with beta blocker and calcium channel blocker treatment or monotherapy with disopyramide or ranolazine were excluded. Patients with a known infiltrative or storage disorder causing cardiac hypertrophy that mimicked obstructive HCM, such as Fabry disease, amyloidosis, or Noonan syndrome with left ventricular hypertrophy, were also excluded.

Patients were randomized in a 1:1 ratio to receive either a starting dose of 5 mg of CAMZYOS or placebo once daily for 30 weeks. Treatment assignment was stratified by baseline NYHA functional class, baseline use of beta blockers, and type of ergometer (treadmill or exercise bicycle).

Groups were well matched with respect to age (mean 59 years), BMI (mean 30 kg/m^2), heart rate (mean 62 bpm), blood pressure (mean 128/76 mmHg), and race (90% Caucasian). Males comprised 54% of the CAMZYOS group and 65% of the placebo group.

At baseline, approximately 73% of the randomized patients were NYHA class II and 27% were NYHA class III. The mean LVEF was 74%, and the mean Valsalva LVOT gradient was 73 mmHg. About 10% had prior septal reduction therapy, 75% were on beta blockers, 17% were on calcium channel blockers, and 14% had a history of atrial fibrillation.

All patients were initiated on CAMZYOS 5 mg (or matching placebo) once daily, and the dose was periodically adjusted to optimize patient response (decrease in LVOT gradient with Valsalva maneuver) and maintain LVEF ≥50%. The dose was also informed by plasma concentrations of CAMZYOS.

In the CAMZYOS group, at the end of treatment, 49% of patients were receiving the 5-mg dose, 33% were receiving the 10-mg dose, and 11% were receiving the 15-mg dose. Three patients temporarily interrupted their dose due to LVEF <50%, of whom two resumed treatment at the same dose and one had the dose reduced from 10 mg to 5 mg.

Primary endpoint

The primary composite functional endpoint, assessed at 30 weeks, was defined as the proportion of patients who achieved either improvement of peak oxygen consumption (pVO2) by ≥1.5 mL/kg/min plus improvement in NYHA class by at least 1 or improvement of pVO2 by ≥3.0 mL/kg/min plus no worsening in NYHA class.

A greater proportion of patients met the primary endpoint at Week 30 in the CAMZYOS group compared to the placebo group (37% vs. 17%, respectively, p=0.0005; see Table 2).

Table 2: Primary Endpoint at 30 Weeks
 | CAMZYOS; n (%); N = 123 | Placebo; n (%); N = 128 | Difference; (95% CI) | p-value
Total responders | 45 (37%) | 22 (17%) | 19% (9, 30) | 0.0005
Change from baseline; pVO2 ≥1.5 mL/kg/min and; decreased NYHA | 41 (33%) | 18 (14%) | 19% (9, 30)
Change from baseline; pVO2 ≥3 mL/kg/min and; NYHA not increased | 29 (23%) | 14 (11%) | 13% (3, 22)

A range of demographic characteristics, baseline disease characteristics, and baseline concomitant medications were examined for their influence on outcomes. Results of the primary analysis consistently favored CAMZYOS across all subgroups analyzed (Figure 4).

Figure 4: Subgroup Analysis of the Primary Composite Functional Endpoint

The dashed vertical line represents the overall treatment effect and the solid vertical line (no effect) indicates no difference between treatment groups.
Note: The figure above presents effects in various subgroups, all of which are baseline characteristics. The 95% confidence limits that are shown do not take into account the number of comparisons made and may not reflect the effect of a particular factor after adjustment for all other factors. Apparent homogeneity or heterogeneity among groups should not be over-interpreted.

Although the benefit of mavacamten was smaller in patients on background beta blocker therapy compared to those who were not (attenuated improvement in pVO2), analyses of other secondary endpoints (symptoms, LVOT gradient) suggest that patients might benefit from mavacamten treatment regardless of beta blocker use.

Secondary endpoints

The treatment effects of CAMZYOS on LVOT obstruction, functional capacity, and health status were assessed by change from baseline through Week 30 in post-exercise LVOT peak gradient, change in pVO2, proportion of patients with improvement in NYHA class, Kansas City Cardiomyopathy Questionnaire-23 (KCCQ-23) Clinical Summary Score (CSS), and Hypertrophic Cardiomyopathy Symptom Questionnaire (HCMSQ) Shortness of Breath (SoB) domain score. At Week 30, patients receiving CAMZYOS had greater improvement compared to the placebo group across all secondary endpoints (Table 3, Figure 5, Figure 6, Table 4, and Figures 7-10).

Table 3: Change from Baseline to Week 30 in Post-Exercise LVOT Gradient, pVO2, and NYHA Class
 | CAMZYOS; N=123 | Placebo; N=128 | Difference (95% CI) | p-value
Post-Exercise LVOT; gradient (mmHg), mean; (SD) | -47 (40) | -10 (30) | -35 (-43, -28) | <0.0001
pVO2 (mL/kg/min), mean; (SD) | 1.4 (3.1) | -0.1 (3.0) | 1.4 (0.6, 2.1) | <0.0006
Number (%) with NYHA; Class improved ≥1 | 80 (65%) | 40 (31%) | 34% (22%, 45%) | <0.0001

Figure 5: Cumulative Distribution of Change from Baseline to Week 30 in LVOT Peak Gradient

Figure 6: Cumulative Distribution of Change from Baseline to Week 30 in pVO2

Table 4: Change from Baseline to Week 30 in KCCQ-23 CSS and HCMSQ SoB Domain
 | Baseline, Mean (SD) |  | Change from Baseline to Week 30, Mean; (SD) |  | Difference,; LS Mean; (95%CI) and; p-value
 | CAMZYOS | Placebo | CAMZYOS | Placebo | Difference,; LS Mean; (95%CI) and; p-value
KCCQ‑23 CSS† | n=99; 71 (16) | n=97; 71 (19) | 14 (14) | 4 (14) | 9 (5, 13); p<0.0001
KCCQ-23 TSS | 71 (17) | 69 (22) | 12 (15) | 5 (16)
KCCQ-23 PL | 70 (18) | 72 (19) | 15 (17) | 4 (15)
HCMSQ SoB‡ | n=108; 5 (3) | n=109; 5 (3) | -3 (3) | -1 (2) | -2 (-2, -1); p<0.0001
†The KCCQ‑23 CSS is derived from the Total Symptom Score (TSS) and the Physical Limitations (PL) score of the KCCQ‑23. The CSS ranges from 0 to 100 with higher scores representing less severe symptoms and/or physical limitations.
‡The HCMSQ SoB domain score measures the frequency and severity of shortness of breath. The HCMSQ SoB domain score ranges from 0 to 18 with lower scores representing less shortness of breath.
Missing data were not imputed to summarize the baseline and change from baseline to Week 30 values. Difference in mean change from baseline between treatment groups was estimated using a mixed model for repeated measures.

Figure 7 shows the time course for changes in KCCQ-23 CSS. Figure 8 shows the distribution of changes from baseline to Week 30 for KCCQ-23 CSS.

Figure 7: KCCQ-23 Clinical Summary Score: Mean Change from Baseline Over Time

Figure 8: KCCQ-23 Clinical Summary Score: Cumulative Distribution of Change from Baseline to Week 30

Figure 9 shows the time course for changes in HCMSQ SoB. Figure 10 shows the distribution of changes from baseline to Week 30 for HCMSQ SoB.

Figure 9: HCMSQ Shortness of Breath Domain: Mean Change from Baseline Over Time

Figure 10: HCMSQ Shortness of Breath Domain: Cumulative Distribution of Change from Baseline to Week 30

VALOR-HCM

The efficacy of CAMZYOS was evaluated in VALOR-HCM, a Phase 3, double-blind, randomized, 16-week, placebo-controlled trial in 112 patients (mean age of 60 years; 51% men; 93% ≥NYHA class III) randomized 1:1 to receive treatment with CAMZYOS or placebo. At baseline, all patients had symptomatic obstructive HCM and were SRT eligible.

Patients with severely symptomatic drug-refractory obstructive HCM (including 33% on any combination of beta-blocker, calcium channel blocker and/or disopyramide; 20% were on disopyramide alone or in combination with other treatment), and NYHA class III/IV or class II with exertional syncope or near syncope, were included in the study. Patients were required to have LVOT peak gradient ≥50 mmHg at rest or with provocation, and LVEF ≥60%. Patients must have been referred or under active consideration within the past 12 months for SRT and actively considering scheduling the procedure.

Patients received CAMZYOS (2.5 mg, 5 mg, 10 mg, or 15 mg) or a placebo capsule once daily for 16 weeks. Dose adjustment was based on clinical echocardiogram parameters.

Primary endpoint

CAMZYOS was shown to be superior to placebo in reducing the proportion of patients who met the primary endpoint (the composite of patient decision to proceed with SRT prior to or at Week 16 or met SRT eligibility (LVOT gradient of ≥50 mmHg and NYHA class III-IV, or class II with exertional syncope or near syncope) at Week 16 (18% vs. 77%, respectively, p<0.0001; see Table 5).

Table 5: Primary Endpoint at 16 Weeks
 | CAMZYOS; n (%); n=56 | Placebo; n (%); n=56 | Treatment difference; (95% CI) | p-value
Primary efficacy composite endpoint | 10 (18) | 43 (77) | 59% (44%, 74%) | <0.0001
Patient decision to proceed with SRT | 2 (3.6) | 2 (3.6)
SRT-eligible based on guideline criteria* | 8 (14) | 39 (70)
SRT status not evaluable (imputed as meeting guideline criteria) | 0 | 2 (3.6)
*NYHA Class III or IV, or Class II with exertion induced syncope or near syncope and dynamic LVOT gradient at rest or with provocation (i.e., Valsalva or exercise) ≥50 mmHg.

Secondary endpoints

The treatment effects of CAMZYOS on LVOT obstruction, functional capacity, and health status were assessed by change from baseline through Week 16 in post-exercise LVOT gradient, proportion of patients with improvement in NYHA class, and KCCQ-23 CSS.

Table 6: Change from Baseline to Week 16 in Secondary Endpoints
 | CAMZYOS; n=56 | Placebo; n=56 | Difference; (95% CI) | p-value
Post-Exercise LVOT gradient (mmHg), mean (SD) | -39; (37) | -2; (29) | -38; (-49, -28) | <0.0001
Number (%) with NYHA Class improved ≥1 | 35; (63%) | 12; (21%) | 41%; (25%, 58%) | <0.0001
KCCQ-23 CSS†, mean (SD) | 10; (16) | 2; (12) | 9; (5, 14) | <0.0001
KCCQ-23 TSS, mean (SD) | 10; (16) | 2; (14) | 10; (5, 15)
KCCQ-23 PL, mean (SD) | 10; (19) | 2; (17) | 10; (5, 16)
†The KCCQ-23 CSS is derived from the Total Symptom Score (TSS) and the Physical Limitations (PL) score of the KCCQ-23. The CSS ranges from 0 to 100 with higher scores representing less severe symptoms and/or physical limitations.

Figure 11 shows the time course for changes in KCCQ-23 CSS. Figure 12 shows the distribution of changes from baseline to Week 16 for KCCQ-23 CSS.

Figure 11: KCCQ-23 Clinical Summary Score: Mean Change from Baseline Over Time

Figure 12: KCCQ-23 Clinical Summary Score: Cumulative Distribution of Change from Baseline to Week 16
The figure displays the cumulative percentage of patients achieving a certain level of response.

16 HOW SUPPLIED/STORAGE AND HANDLING

CAMZYOS® is supplied as immediate release Size 2 hard gelatin capsules containing 2.5 mg, 5 mg, 10 mg, or 15 mg of mavacamten. White opaque capsule bodies are imprinted with “Mava”, and the opaque cap is imprinted with the strength. The capsule contains white to off-white powder. CAMZYOS capsules are available in bottles of 30 capsules, as listed in the table below:

Strength | Capsule Cap | NDC Number
2.5 mg | Light purple | 73625-111-11
5 mg | Yellow | 73625-112-11
10 mg | Pink | 73625-113-11
15 mg | Gray | 73625-114-11

Storage

Store at 20°C to 25°C (68°F to 77°F), excursions permitted between 15°C and 30°C (between 59°F and 86°F) [see USP Controlled Room Temperature].

17 PATIENT COUNSELING INFORMATION

Advise the patient and/or caregiver to read the FDA-approved patient labeling (Medication Guide).

Heart Failure

Inform patients that cardiac function monitoring must be performed using echocardiography to monitor for heart failure [see Warnings and Precautions (5.1)]. Advise patients to report any signs or symptoms of heart failure immediately to their healthcare provider.

Drug Interactions

Advise patients to inform their healthcare providers of all concomitant products, including over-the-counter medications (such as omeprazole, esomeprazole, or cimetidine) and supplements, prior to and during CAMZYOS treatment.

CAMZYOS REMS Program

CAMZYOS is available only through a restricted program called the CAMZYOS REMS Program [see Warnings and Precautions (5.3)]. Inform the patient of the following notable requirements:

- Patients must enroll in the program and comply with ongoing monitoring requirements [see Warnings and Precautions 5.1 and 5.3].

CAMZYOS is only prescribed by certified healthcare providers and only dispensed from certified pharmacies participating in the program. Provide patients with the telephone number and website for information on how to obtain the product [see Warnings and Precautions (5.3)].

Embryo-Fetal Toxicity

Advise pregnant females and females of reproductive potential of the potential risk to a fetus. Advise females of reproductive potential to inform their healthcare provider of a known or suspected pregnancy [see Warnings and Precautions (5.4) and Use in Specific Populations (8.1, 8.3)].

Advise females of reproductive potential to use effective contraception during treatment with CAMZYOS and for 4 months after the last dose.

CHCs containing a combination of ethinyl estradiol and norethindrone may be used with mavacamten. However, CAMZYOS may reduce the effectiveness of certain other combined hormonal contraceptives (CHC). If these CHCs are used, advise patients to add nonhormonal contraception (such as condoms) during concomitant use and for 4 months after the last dose of CAMZYOS [see Drug Interactions (7.2) and Use in Specific Populations (8.3)].

Advise females who are exposed to CAMZYOS during pregnancy that there is a pregnancy safety study that monitors pregnancy outcomes. Encourage these patients to report their pregnancies to Bristol-Myers Squibb at 1-800-721-5072 or www.bms.com.

Instructions for Taking CAMZYOS

CAMZYOS capsules should be swallowed whole. Advise patients that if they miss a dose of CAMZYOS, to take the dose as soon as possible that day and the next scheduled dose should be taken at the usual time the following day. The patient should not take two doses in the same day.

Marketed by:
Bristol-Myers Squibb Company
Princeton, NJ 08543 USA

CAMZYOS® is a trademark of MyoKardia, Inc., a Bristol Myers Squibb company.

Medication Guide

CAMZYOS® (kam-zai-ōs)

(mavacamten)

capsules, for oral use

What is the most important information I should know about CAMZYOS?

CAMZYOS may cause serious side effects, including:

- Heart failure, a condition where the heart cannot pump with enough force. Heart failure is a serious condition that can lead to death. You must have echocardiograms before you take your first dose and during your treatment with CAMZYOS to help your healthcare provider understand how your heart is responding to CAMZYOS. People who develop a serious infection or irregular heartbeat have a greater risk of heart failure during treatment with CAMZYOS.
Tell your healthcare provider or get medical help right away if you develop new or worsening:

o shortness of breath

o swelling in your legs

o chest pain

o a racing sensation in your heart (palpitations)

o fatigue

o rapid weight gain

- The risk of heart failure is also increased when CAMZYOS is taken with certain other medicines. Tell your healthcare provider about the medicines you take, both prescribed and obtained over-the-counter, before and during treatment with CAMZYOS.
- Because of the serious risk of heart failure, CAMZYOS is only available through a restricted program called the CAMZYOS Risk Evaluation and Mitigation Strategy (REMS) Program.
  - Your healthcare provider must be enrolled in the CAMZYOS REMS Program in order for you to be prescribed CAMZYOS.
  - Before you take CAMZYOS, you must enroll in the CAMZYOS REMS Program. Talk to your healthcare provider about how to enroll in the CAMZYOS REMS Program. You will be given information about the program when you enroll.
  - Before you take CAMZYOS, your healthcare provider and pharmacist will make sure you understand how to take CAMZYOS safely, which will include returning for echocardiograms when advised by your healthcare provider.
CAMZYOS can only be dispensed by a certified pharmacy that participates in the CAMZYOS REMS Program. Your healthcare provider can give you information on how to find a certified pharmacy. You will not be able to get CAMZYOS at a local pharmacy.
  - If you have questions about the CAMZYOS REMS Program, ask your healthcare provider, go to www.CAMZYOSREMS.com, or call 1-833-628-7367.

See “What are the possible side effects of CAMZYOS?” for information about side effects.

What is CAMZYOS?

CAMZYOS is a prescription medicine used to treat adults with symptomatic obstructive hypertrophic cardiomyopathy (HCM). CAMZYOS may improve your symptoms and your ability to be active. It is not known if CAMZYOS is safe and effective in children.

Before taking CAMZYOS, tell your healthcare provider about all of your medical conditions, including if you:

- are pregnant or plan to become pregnant. CAMZYOS may harm your unborn baby. Tell your healthcare provider right away if you become pregnant or think you may be pregnant during treatment with CAMZYOS. You may also report your pregnancy by calling Bristol-Myers Squibb at 1-800-721-5072 or www.bms.com.
If you are a female and able to become pregnant:
- Your healthcare provider will do a pregnancy test before you start treatment with CAMZYOS.
- You should use effective birth control (contraception) during treatment with CAMZYOS and for 4 months after your last dose of CAMZYOS.
- CAMZYOS may reduce how well some hormonal birth control works. Talk to your healthcare provider about the use of effective forms of birth control during treatment with CAMZYOS.
- are breastfeeding or plan to breastfeed. It is not known if CAMZYOS passes into your breast milk. Talk to your healthcare provider about the best way to feed your baby during treatment with CAMZYOS.

Before and during CAMZYOS treatment, tell your healthcare provider about all the medicines you take, including prescription and over-the-counter medicines, vitamins, and herbal supplements. Taking CAMZYOS with certain medicines or grapefruit juice may cause heart failure. Do not stop or change the dose of a medicine or start a new medicine without telling your healthcare provider.

Especially tell your healthcare provider if you:

- Take over-the-counter medicines such as omeprazole (for example, Prilosec), esomeprazole (for example, Nexium), or cimetidine (for example, Tagamet).
- Take other medicines to treat your obstructive HCM disease.
- Develop an infection.

How should I take CAMZYOS?

- Take CAMZYOS exactly as your healthcare provider tells you to take it.
- Do not change your dose of CAMZYOS without talking to your healthcare provider first.
- Take CAMZYOS 1 time a day.
- Swallow the capsule whole. Do not break, open, or chew the capsule.
- If you miss a dose of CAMZYOS, take it as soon as possible and take your next dose at your regularly scheduled time the next day. Do not take 2 doses on the same day to make up for a missed dose.
- Your healthcare provider may change your dose, temporarily stop, or permanently stop your treatment with CAMZYOS if you have certain side effects.
- If you take too much CAMZYOS, call your healthcare provider or go to the nearest hospital emergency room right away.

What are the possible side effects of CAMZYOS?

CAMZYOS may cause serious side effects, including:

- Heart failure. See “What is the most important information I should know about CAMZYOS?”

The most common side effects of CAMZYOS include: dizziness and fainting (syncope).

These are not all of the possible side effects of CAMZYOS.

Call your doctor for medical advice about side effects. You may report side effects to FDA at 1-800-FDA-1088.

You may also report side effects to Bristol-Myers Squibb at 1-800-721-5072.

How should I store CAMZYOS?

Store CAMZYOS at room temperature between 68°F to 77°F (20°C to 25°C).

Keep CAMZYOS and all medicines out of the reach of children.

General information about the safe and effective use of CAMZYOS.

Medicines are sometimes prescribed for purposes other than those listed in a Medication Guide. Do not use CAMZYOS for a condition for which it was not prescribed. Do not give CAMZYOS to other people, even if they have the same symptoms you have. It may harm them. You can ask your healthcare provider or pharmacist for information about CAMZYOS that is written for health professionals.

What are the ingredients in CAMZYOS?

Active ingredient: mavacamten

Inactive ingredients: croscarmellose sodium, hypromellose, magnesium stearate (non-bovine), mannitol, and silicon dioxide. The capsule contains black iron oxide, gelatin, red iron oxide, titanium dioxide, and yellow iron oxide.

Marketed by:

Bristol-Myers Squibb Company
Princeton, NJ 08543 USA

CAMZYOS® is a trademark of MyoKardia, Inc., a Bristol Myers Squibb company.

For more information, go to www.CAMZYOS.com or call 1-800-721-5072.

This Medication Guide has been approved by the U.S. Food and Drug Administration.

Revised: 04/2025

CAMZYOS 2.5 mg Label

NDC 73625-111-11

Rx only

CAMZYOS™

(mavacamten)

capsules

2.5 mg

Dispense the enclosed Medication Guide to each patient.

Recommended Dosage: See Prescribing Information

Keep out of reach of children.

Do not use if inner seal bottle is broken or missing.

30 Capsules

Bristol Myers Squibb

CAMZYOS 5 mg Label

NDC 73625-112-11

Rx only

CAMZYOS™

(mavacamten)

capsules

5 mg

Dispense the enclosed Medication Guide to each patient.

Recommended Dosage: See Prescribing Information

Keep out of reach of children.

Do not use if inner seal bottle is broken or missing.

30 Capsules

Bristol Myers Squibb

CAMZYOS 10 mg Label

NDC 73625-113-11

Rx only

CAMZYOS™

(mavacamten)

capsules

10 mg

Dispense the enclosed Medication Guide to each patient.

Recommended Dosage: See Prescribing Information

Keep out of reach of children.

Do not use if inner seal bottle is broken or missing.

30 Capsules

Bristol Myers Squibb

CAMZYOS 15 mg Label

NDC 73625-114-11

Rx only

CAMZYOS™

(mavacamten)

capsules

15 mg

Dispense the enclosed Medication Guide to each patient.

Recommended Dosage: See Prescribing Information

Keep out of reach of children.

Do not use if inner seal bottle is broken or missing.

30 Capsules

Bristol Myers Squibb